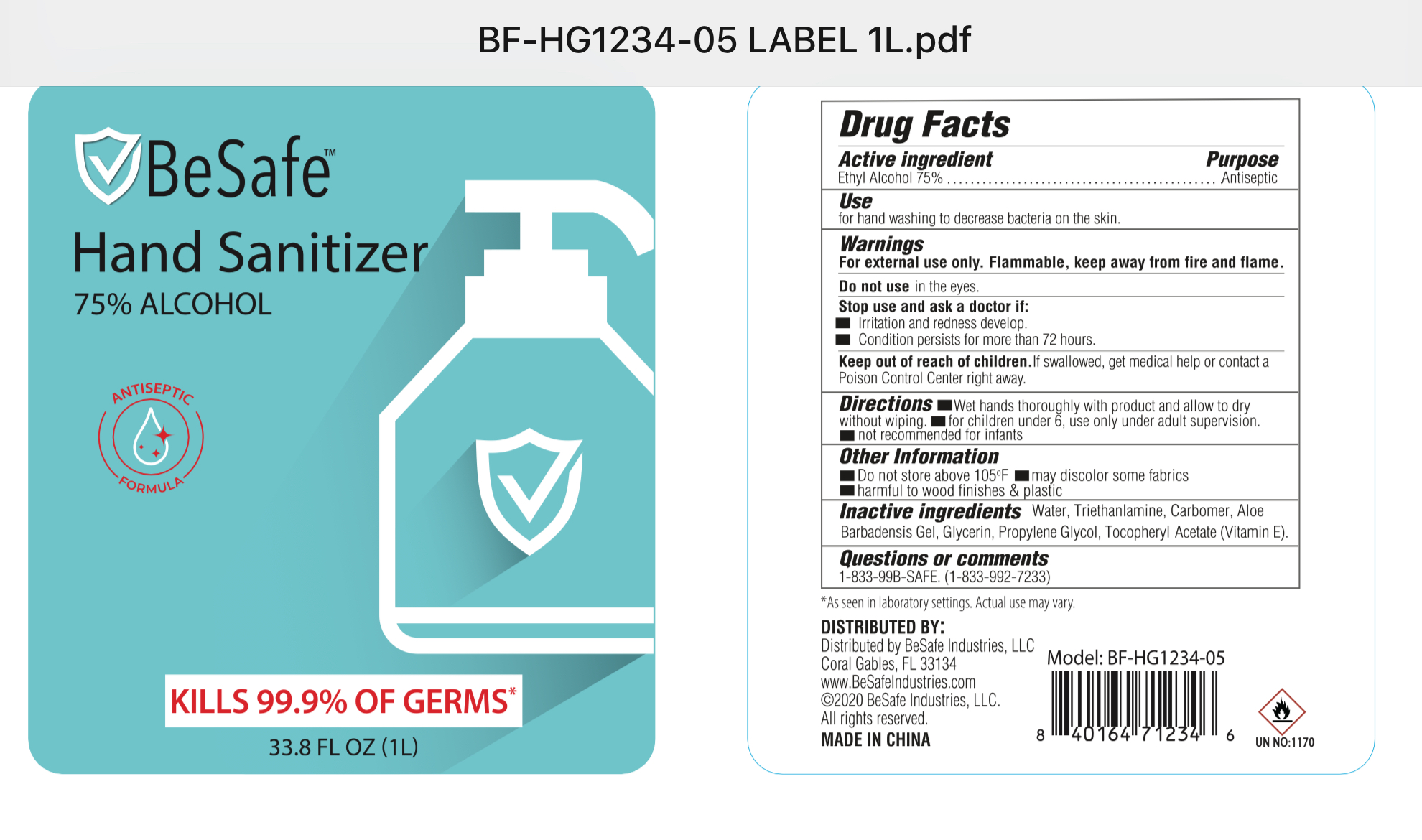 DRUG LABEL: BeSafe Hand Sanitizer
NDC: 77693-001 | Form: SOLUTION
Manufacturer: Besafe Industries LLC
Category: otc | Type: HUMAN OTC DRUG LABEL
Date: 20200714

ACTIVE INGREDIENTS: ALCOHOL 75 mL/100 mL
INACTIVE INGREDIENTS: GLYCERIN; CARBOMER 940; TROLAMINE; ALOE VERA WHOLE; PROPYLENE GLYCOL; .ALPHA.-TOCOPHEROL ACETATE

Active Ingredient(s)

Alcohol 75% v/v. Purpose: Antiseptic

Purpose

Antiseptic

Use

For hand washing to decrease bacterial on the skin

Warnings

For external use only. Flammable. Keep away from fire and flame.

Do not use in the eyes

Stop use and ask a doctor if

- irritation and redness develop
- condition persists for more then 72 hours

Keep out of reach of children. If swallowed, get medical help or contact a Poison Control Center right away.

Directions

Wet hands thoroughly with product and allow to dry without wiping

For children under 6, use only under adults supervision

Not reommended for infants

Other information

Do not store above 105F

May discolor some fabrics

Harmful to wood finishes and plastics

Inactive ingredients

Water, carbomer, triethanolamine, glycerin, aloe barbadensis gel, propylene glycol, tocopheryl acetate (Vitamin E)